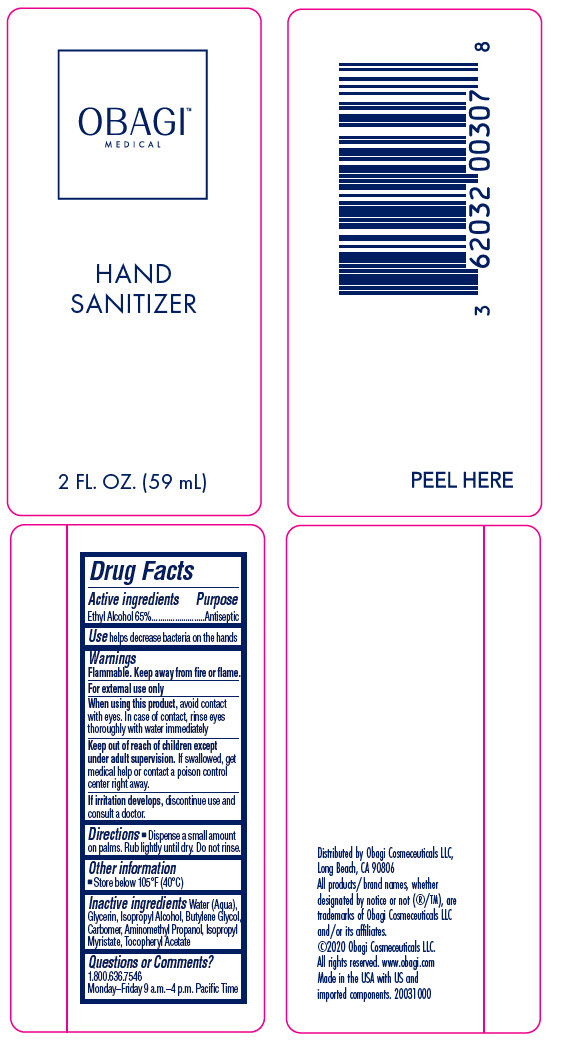 DRUG LABEL: OBAGI MEDICAL HAND SANITIZER
NDC: 62032-003 | Form: GEL
Manufacturer: OBAGI COSMECEUTICALS LLC
Category: otc | Type: HUMAN OTC DRUG LABEL
Date: 20200702

ACTIVE INGREDIENTS: ALCOHOL 65 mL/100 mL
INACTIVE INGREDIENTS: WATER; GLYCERIN; ISOPROPYL ALCOHOL; BUTYLENE GLYCOL; CARBOMER HOMOPOLYMER, UNSPECIFIED TYPE; AMINOMETHYLPROPANOL; ISOPROPYL MYRISTATE; .ALPHA.-TOCOPHEROL ACETATE

OBAGI™ MEDICAL HAND SANITIZER

Drug Facts

Active ingredients

Ethyl Alcohol 65%

Purpose

Antiseptic

Use

helps decrease bacteria on the hands

Warnings

Flammable. Keep away from fire or flame.

For external use only

When using this product, avoid contact with eyes. In case of contact, rinse eyes thoroughly with water immediately

Keep out of reach of children except under adult supervision. If swallowed, get medical help or contact a poison control center right away.

STOP USE

If irritation develops, discontinue use and consult a doctor.

Directions

- Dispense a small amount on palms. Rub lightly until dry. Do not rinse.

Other information

- Store below 105°F (40°C)

Inactive ingredients

Water (Aqua), Glycerin, Isopropyl Alcohol, Butylene Glycol, Carbomer, Aminomethyl Propanol, Isopropyl Myristate, Tocopheryl Acetate

Questions or Comments?

1.800.636.7546

Monday–Friday 9 a.m.–4 p.m. Pacific Time

Distributed by Obagi Cosmeceuticals LLC,
Long Beach, CA 90806

PRINCIPAL DISPLAY PANEL - 59 mL Bottle Label

OBAGI™
MEDICAL

HAND
SANITIZER

2 FL. OZ. (59 mL)